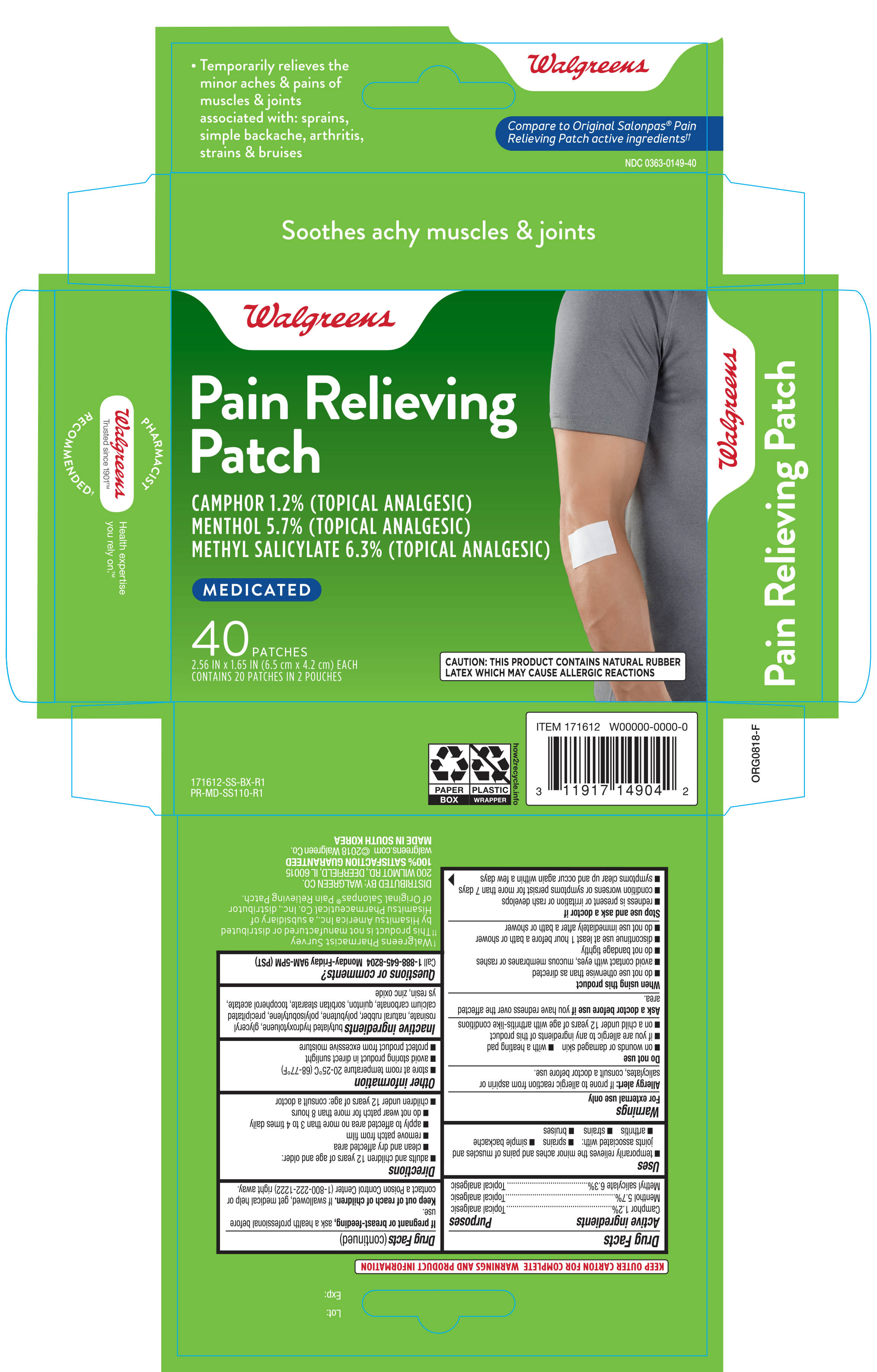 DRUG LABEL: WALGREENS MEDICATED PAIN RELIEVING
NDC: 0363-0149 | Form: PATCH
Manufacturer: WALGREENS
Category: otc | Type: HUMAN OTC DRUG LABEL
Date: 20190109

ACTIVE INGREDIENTS: CAMPHOR (SYNTHETIC) 7.1 mg/1 1; MENTHOL 33 mg/1 1; METHYL SALICYLATE 36 mg/1 1
INACTIVE INGREDIENTS: BUTYLATED HYDROXYTOLUENE; NATURAL LATEX RUBBER; CALCIUM CARBONATE; SORBITAN MONOSTEARATE; ZINC OXIDE

Walgreens Medicated Pain Relieving Patch 40ct (171612, 2019)

Active ingredients Purpose

Camphor 1.2%......................................................................................Topical Analgesic

Menthol 5.7%........................................................................................Topical Analgesic

Methyl Salicylate 6.3%...........................................................................Topical Analgesic

Uses

For temporary relief of minor aches and pains of muscles and joints associated with

- arthritis
- simple backache
- strains
- bruises
- sprains

Warnings

For external use only

Allergy alert: If prone to allergic reaction from aspirin or salicylates, consult a doctor before use.

Do not use

- on wounds or damaged skin
- with a heating pad
- if you are allergic to any ingredients of this product
- on a child under 12 years of age with arthritis-like conditions

Ask a doctor before use if you have redness over the affected area.

When using this product

- do not use otherwise than directed
- avoid contact with the eyes, mucous membranes or rashes
- do not bandage tightly
- discontinue use at least 1 hour before a bath or shower
- do not use immediately after a bath or shower

Stop use and ask a doctor if

- redness is present or irritation or rash develops
- conditions worsens or symptoms persist for more than 7 days
- symptoms clear up and occur again within a few days

PREGNANCY OR BREAST FEEDING

If pregnant or breast-feeding, ask a health professional before use.

Keep out of reach of children. If swallowed, get medical help or contact a Poison Control Center (1-800-222-1222) right away.

Directions

Adults and children 12 years of age and over:

- clean and dry affected area
- remove patch from film
- apply to affected area no more than 3 to 4 times daily
- do not wear patch for more than 8 hours
- Children under 12 years of age: Consult a doctor

Other information

- store at room temperature 20-25°C (68-77°F)
- avoid storing product in direct sunlight
- protect product from excessive moisture

Inactive ingredients

Butylated Hydroxytoluene, Glyceryl Rosinate, Natural Rubber, Polybutene, Polyisobutylene, Precipitated Calcium Carbonate, Quinton, Sorbitan Stearate, Tocopherol Acetate, YS Resin, Zinc Oxide

Questions or comments?

Call 1-888-645-8204 Monday-Friday 9AM-5PM (PST)

DOSAGE AND ADMINISTRATION

DISTRIBUTED BY: WALGREEN CO.

200 WILMOT RD., DEERFIELD, IL 60015

walgreens.com

MADE IN SOUTH KOREA